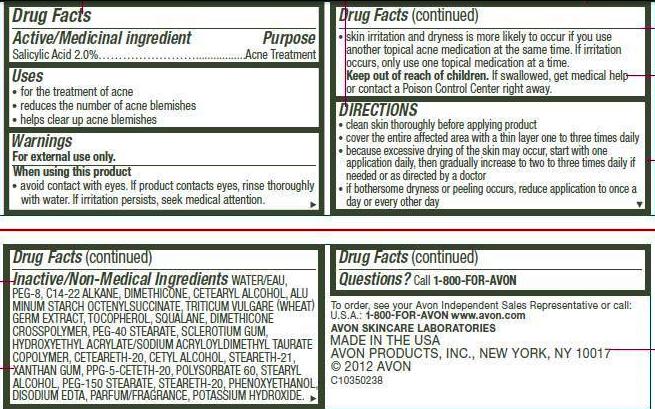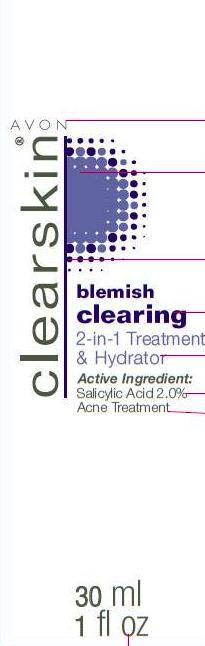 DRUG LABEL: clearskin
NDC: 10096-0278 | Form: LOTION
Manufacturer: Avon Products, Inc.
Category: otc | Type: HUMAN OTC DRUG LABEL
Date: 20120423

ACTIVE INGREDIENTS: SALICYLIC ACID 0.6 mL/30 mL

Drug Facts

Active/Medicinal ingredient
Salicylic Acid 2.0%..................

Purpose
......................Acne Treatment

Uses
• for the treatment of acne
• reduces the number of acne blemishes
• helps clear up acne blemishes

Warnings
For external use only.

When using this product

• avoid contact with eyes. If product contacts eyes, rinse thoroughly with water. If irritation persists, seek medical attention.
• skin irritation and dryness is more likely to occur if you use another topical acne medication at the same time. If irritation occurs, only use one topical medication at a time.

Keep out of reach of children.
• If swallowed, get medical help or contact a Poison Control Center right away.

DIRECTIONS
• clean skin thoroughly before applying product
• cover the entire affected area with a thin layer one to three times daily
• because excessive drying of the skin may occur, start with one application daily, then gradually increase to two to three times daily if needed or as directed by a doctor
• if bothersome dryness or peeling occurs, reduce application to once a day or every other day

INACTIVE INGREDIENT

Inactive/Non-Medical Ingredients WATER/EAU, PEG-8, C14-22 ALKANE, DIMETHICONE, CETEARYL ALCOHOL, ALUMINUM STARCH OCTENYLSUCCINATE, TRITICUM VULGARE (WHEAT) GERM EXTRACT, TOCOPHEROL, SQUALANE, DIMETHICONE CROSSPOLYMER, PEG-40 STEARATE, SCLEROTIUM GUM, HYDROXYETHYL ACRYLATE/SODIUM ACRYLOYLDIMETHYL TAURATE COPOLYMER, CETEARETH-20, CETYL ALCOHOL, STEARETH-21, XANTHAN GUM, PPG-5-CETETH-20, POLYSORBATE 60, STEARYL ALCOHOL, PEG-150 STEARATE, STEARETH-20, PHENOXYETHANOL, DISODIUM EDTA, PARFUM/FRAGRANCE, POTASSIUM HYDROXIDE.

Questions? Call 1-800-FOR-AVON